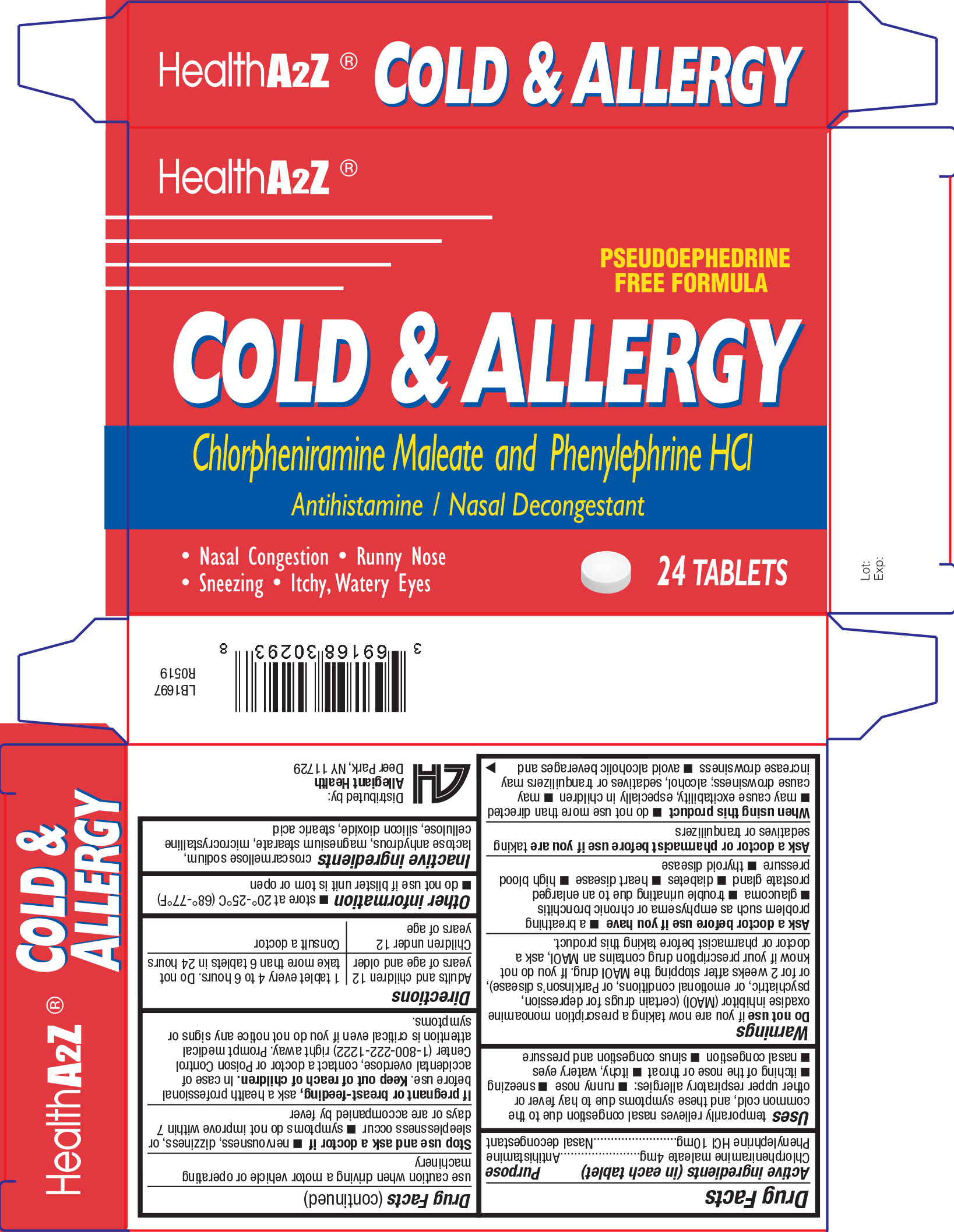 DRUG LABEL: Cold and Allergy
NDC: 69168-406 | Form: TABLET
Manufacturer: Allegiant Health
Category: otc | Type: HUMAN OTC DRUG LABEL
Date: 20191212

ACTIVE INGREDIENTS: PHENYLEPHRINE HYDROCHLORIDE 10 mg/1 1; CHLORPHENIRAMINE MALEATE 4 mg/1 1
INACTIVE INGREDIENTS: SILICON DIOXIDE; MAGNESIUM STEARATE; STEARIC ACID; CROSCARMELLOSE SODIUM; MICROCRYSTALLINE CELLULOSE

Drug Facts

Active ingredients (in each tablet)

Phenylephrine HCl 10 mg
Chlorpheniramine maleate 4mg

Purpose

Nasal Decongestant
Antihistamine

Uses

temporarily relieves nasal congestion due to the common cold, and these symptoms due to hay fever or other upper respiratory allergies:

- runny nose
- sneezing
- itching of the nose or throat
- itchy, watery eyes
- nasal congestion
- sinus congestion and pressure

Warnings

Do Not Use

if you are now taking a prescription monoamine oxadise inhibitor (MAOI) (certain drugs for depression, psychiatric, or emotional conditions, or Parkinson’s disease), or for 2 weeks after stopping the MAOI drug. If you do not know if your prescription drug contains an MAOI, ask a doctor or pharmacist before taking this product.

Ask a doctor before use if you have

- a breathing problem such as emphysema or chronic bronchitis
- glaucoma
- trouble urinating due to an enlarged prostate gland
- diabetes
- heart disease
- high blood pressure
- thyroid disease

Ask a doctor or pharmacist before use if you are

taking sedatives or tranquilizers

When using this product

- do not use more than directed
- may cause excitability, especially in children
- may cause drowsiness; alcohol, sedatives or tranquilizers may increase drowsiness
- avoid alcoholic beverages and use caution when driving a motor vehicle or operating machinery

Stop use and ask a doctor if

- nervousness, dizziness, or sleeplessness occur
- symptoms do not improve within 7 days or are accompanied by fever

If pregnant or breast-feeding

ask a health professional before use.

Keep out of reach of children

In case of accidental overdose, contact a doctor or Poison Control Center (1-800-222-1222) right away. Prompt medical attention is critical even if you do not notice any signs or symptoms.

Directions

Adults and children 12 years of age and older: 1 tablet every 4 to 6 hours. Do not take more than 6 doses in 24 hours
Children under 12 years of age: Consult a doctor

Other Information

- store at room temperature
- do not use if blister unit is torn or open

Inactive Ingredients

croscarmellose sodium, lactose anhydrous, magnesium stearate, microcrystalline cellulose, silicon dioxide, stearic acid

Package/Label Principal Display Panel

Cold and Allergy